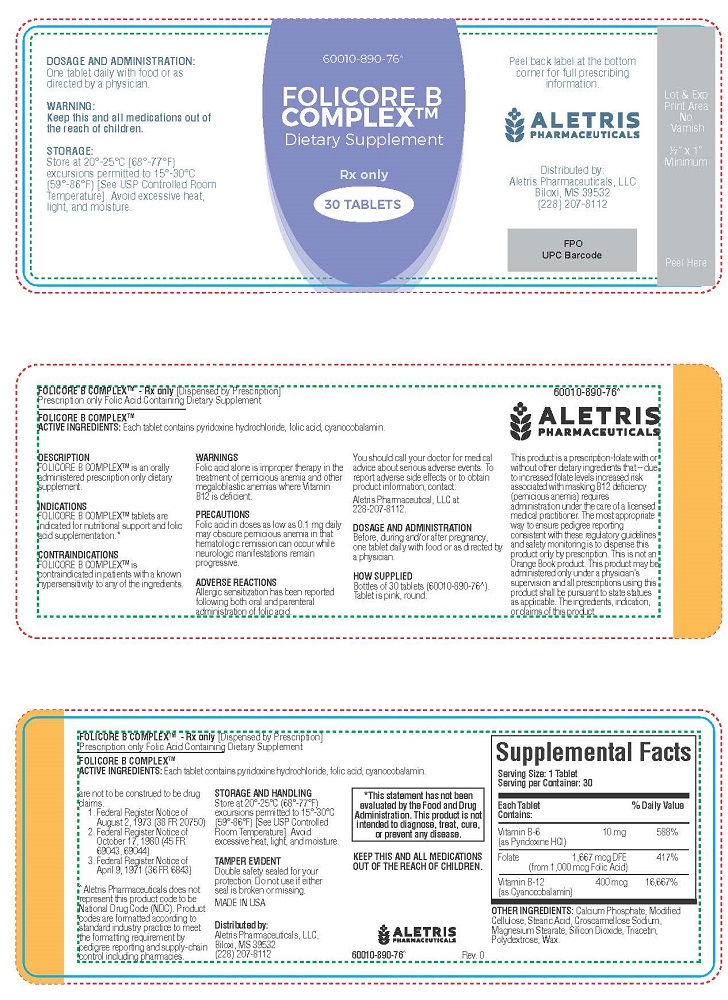 DRUG LABEL: Folicore B Complex
NDC: 86001089076 | Form: TABLET
Manufacturer: Aletris Pharmaceuticals, LLC
Category: other | Type: DIETARY SUPPLEMENT
Date: 20250408

ACTIVE INGREDIENTS: PYRIDOXINE HYDROCHLORIDE 10 mg/1 1; FOLIC ACID 1000 ug/1 1; CYANOCOBALAMIN 400 ug/1 1
INACTIVE INGREDIENTS: CALCIUM PHOSPHATE; STEARIC ACID; CROSCARMELLOSE SODIUM; MAGNESIUM STEARATE; SILICON DIOXIDE; TRIACETIN; POLYDEXTROSE; HYDROXYPROPYL CELLULOSE, UNSPECIFIED; CARNAUBA WAX

FOLICORE B
COMPLEX™
Dietary Supplement

HEALTH CLAIM

FOLICORE B COMPLEXTM - Rx only [Dispensed by Prescription]
Prescription only Folic Acid Containing Dietary Supplement

STATEMENT OF IDENTITY

FOLICORE B COMPLEXTM
ACTIVE INGREDIENTS: Each tablet contains pyridoxine hydrochloride, folic acid, cyanocobalamin.

Serving Size: 1 Tablet; Serving per Container: 30
Each Tablet Contains: |  | % Daily Value
Vitamin B-6 (as Pyridoxine HCl) | 10 mg | 588%
Folate | 1,667 mcg DFE; (from 1,000 mcg Folic Acid) | 417%
Vitamin B-12; (as Cyanocobalamin) | 400 mcg | 16,667%

OTHER INGREDIENTS: Calcium Phosphate, Modified Cellulose, Stearic Acid, Croscarmellose Sodium, Magnesium Stearate, Silicon Dioxide, Triacetin, Polydextrose, Wax.

DESCRIPTION

FOLICORE B COMPLEXTM is an orally administered prescription only dietary supplement.

INDICATIONS

FOLICORE B COMPLEXTM tablets are indicated for nutritional support and folic acid supplementation.

CONTRADINDICATIONS

FOLICORE B COMPLEXTM is contraindicated in patients with a known hypersensitivity to any of the ingredients.

WARNING

Keep this and all medications out of the reach of children.

Folic acid alone is improper therapy in the treatment of pernicious anemia and other megaloblastic anemias where Vitamin B12 is deficient.

ADVERSE REACTIONS

Allergic sensitization has been reported following both oral and parenteral administration of folic acid.

You should call your doctor for medical advice about serious adverse events. To report adverse side effects or to obtain product information, contact: Aletris Pharmaceuticals, LLC at 228-207-8112.

DOSAGE AND ADMINISTRATION

One tablet daily with food or as directed by a physician.

Before, during and/or after pregnancy, one tablet daily with food or as directed by a physician.

PRECAUTION:

Folic acid in doses as low as 0.1 mg daily may obscure pernicious anemia in that hematologic remission can occur while neurologic manifestations remain progressive.

STORAGE

Store at 20°-25°C (68°-77°F) excursions permitted to 15°-30°C (59°-86°F) [See USP Controlled Room Temperature.] Avoid excessive heat, light
and moisture.

HEALTH CLAIM

Distributed by:
Aletris Pharmaceuticals, LLC,
Biloxi, MS 39532
(228) 207-8112